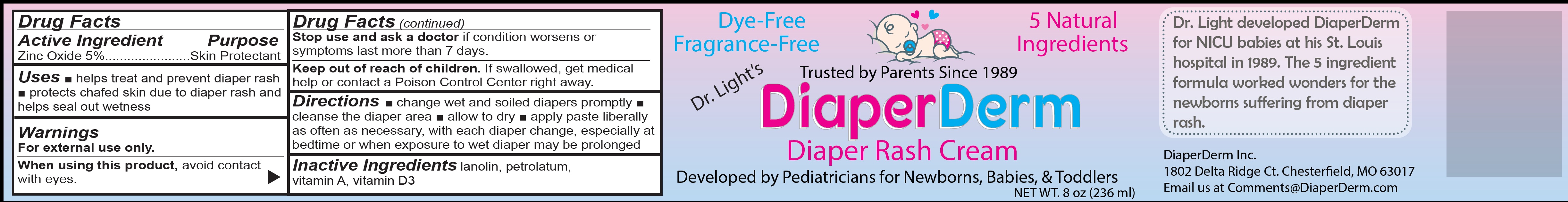 DRUG LABEL: DiaperDerm Diaper Rash
NDC: 80651-093 | Form: CREAM
Manufacturer: Diaperderm Inc
Category: otc | Type: HUMAN OTC DRUG LABEL
Date: 20231106

ACTIVE INGREDIENTS: ZINC OXIDE 50 mg/1 mL
INACTIVE INGREDIENTS: LANOLIN; PETROLATUM; VITAMIN A; CHOLECALCIFEROL

DiaperDerm Diaper Rash Cream

Active Ingredient

Zinc Oxide 5%

Purpose

Skin Protectant

Uses:

- helps treat and prevent diaper rash
- protects chafed skin due to diaper rash and helps seal out wetness

Warnings

For external use only.

When using this product,

avoid contact with eyes.

Stop use and ask a doctor

if condition worsens or symptoms last more than 7 days.

Keep out of reach of children.

- If swallowed, get medical help or contact a Poison Control Center right away.

Directions

- change wet and soiled diapers promptly
- cleanse the diaper area
- allow to dry
- apply paste liberally as often as necessary, with each diaper change, especially at bedtime or when exposure to wet diaper may be prolonged

Inactive Ingredients

lanolin, petrolatum, vitamin A, vitamin D3